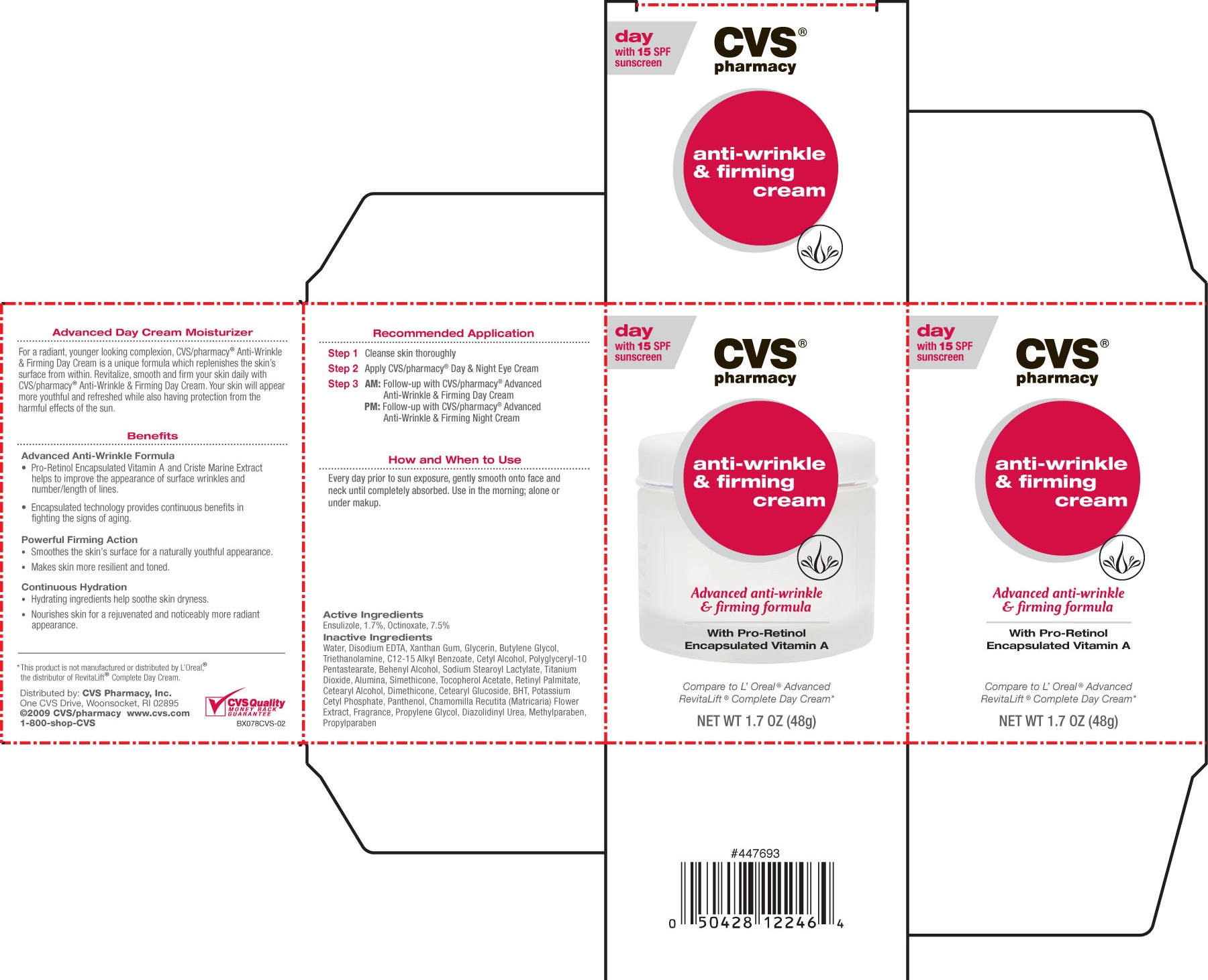 DRUG LABEL: CVS Revitalift Complete with SPF-15
NDC: 59779-264 | Form: LOTION
Manufacturer: CVS Pharmacy
Category: otc | Type: HUMAN OTC DRUG LABEL
Date: 20100719

ACTIVE INGREDIENTS: ENSULIZOLE 17 mg/1 g; OCTINOXATE 75 mg/1 g
INACTIVE INGREDIENTS: WATER; GLYCERIN; EDETATE DISODIUM; XANTHAN GUM; TITANIUM DIOXIDE; BUTYLENE GLYCOL; ALUMINUM OXIDE; DIMETHICONE; STEARYL ALCOHOL; TROLAMINE; CETYL ALCOHOL; SODIUM STEAROYL LACTYLATE; DOCOSANOL; ALPHA-TOCOPHEROL; VITAMIN A PALMITATE; CETOSTEARYL ALCOHOL; PANTHENOL; CETEARYL GLUCOSIDE; PROPYLPARABEN; METHYLPARABEN; DIAZOLIDINYL UREA; BUTYLATED HYDROXYTOLUENE; POTASSIUM CETYL PHOSPHATE; CHAMAEMELUM NOBILE FLOWER

drug facts

Active Ingredients:
Ensulizole, 1.7%, Octinoxate, 7.5%

PURPOSE

Advanced Day Cream Moisturizer
For a radiant, younger looking complexion, CVS/pharmacy Anti-Wrinkle and Firming Day Cream
is a unique formula which replenishes the skin's surface from within. Revitalize, smooth and firm
your skin daily with CVS/pharmacy Anti-wrinkle and firming day cream. Your skin will appear more
youthful and refreshed whil also having protection from the harmful effects of the sun.
Benefits
Advanced Anti-Wrinkle Formula
- Pro-Retinol Encapsulated Vitamin A and Criste Marine Extract helps to improve the appearance
of surface wrinkles and number/length of lines.
- Encapsulated technology provides continuous benefits in fighting the signs of aging
Powerful Firming Action
- Smooths the skin's surface for a naturally youthful appearance.
- Makes skin more resilient and toned
Continuous Hydration
- Hydrating ingredients help soothe skin dryness.
- Nourishes skin for a rejuvenated and noticeably more radiant appearance.

KEEP OUT OF REACH OF CHILDREN

Warnings: None listed

INDICATIONS AND USAGE

Advanced Day Cream Moisturizer
For a radiant, younger looking complexion, CVS/pharmacy Anti-Wrinkle and Firming Day Cream
is a unique formula which replenishes the skin's surface from within. Revitalize, smooth and firm
your skin daily with CVS/pharmacy Anti-wrinkle and firming day cream. Your skin will appear more
youthful and refreshed whil also having protection from the harmful effects of the sun.
Benefits
Advanced Anti-Wrinkle Formula
- Pro-Retinol Encapsulated Vitamin A and Criste Marine Extract helps to improve the appearance
of surface wrinkles and number/length of lines.
- Encapsulated technology provides continuous benefits in fighting the signs of aging
Powerful Firming Action
- Smooths the skin's surface for a naturally youthful appearance.
- Makes skin more resilient and toned
Continuous Hydration
- Hydrating ingredients help soothe skin dryness.
- Nourishes skin for a rejuvenated and noticeably more radiant appearance.

Warnings
None listed

DOSAGE AND ADMINISTRATION

Recommended Application
Step 1 Cleanse skin thoroughly
Step 2 Apply CVS/Pharmacy Day and NIght Cream
Step 3 AM: Follow-up with CVS?Pharmacy Advanced Anti-Wrinkle and Firming Day Cream
PM: Follow-up with CVS/Pharmacy Advanced Anti-Wrinkle and Firming Night Cream
How and When to Use
Every day prior to sun exposure, gently smooth onto face and neck until completely absorbed. Use in the morning; alone or under makeup.

Inactive Ingredients
Water, Disodium EDTA, Xanthan Gum, Glycerin, Butylene Glycol, Triethanolamine,
C12-15 Alkyl Benzoate, Cetyl Alcohol, Polyglyceryl-10 Pentastearate, Behenyl Alcohol,
Sodium Stearoyl Lactylate, Titanium Dioxide, Alumina, Simethicone, Tocopherol Acetate,
Retinyl Palmitate, Cetearyl Alcohol, Dimethicone, Cetearyl Glucoside, BHT, Potassium
Cetyl Phosphate, Panthenol, Chamomilla Recutita (Matricaria) Flower Extract,
Fragrance, Propylene Glycol, Diazolidinyl Urea, Methylparaben, Propylparaben